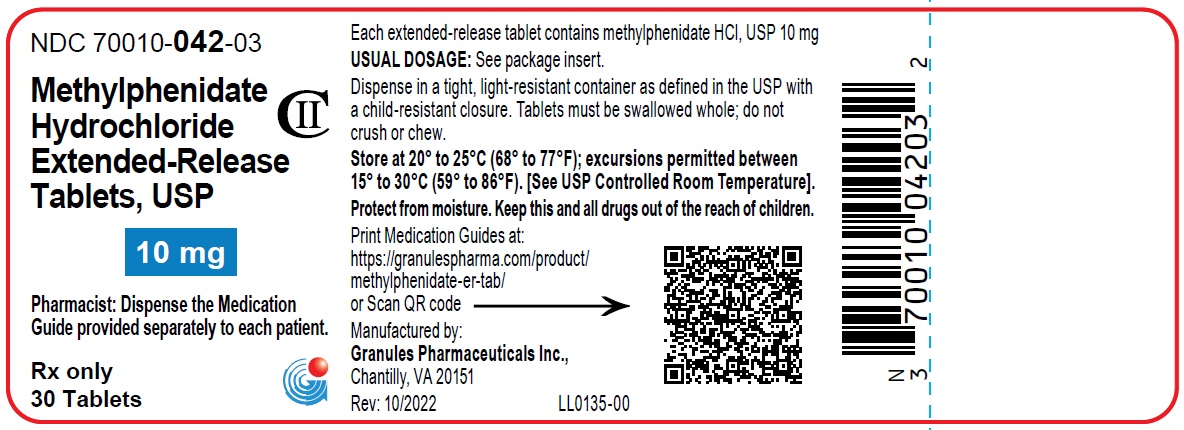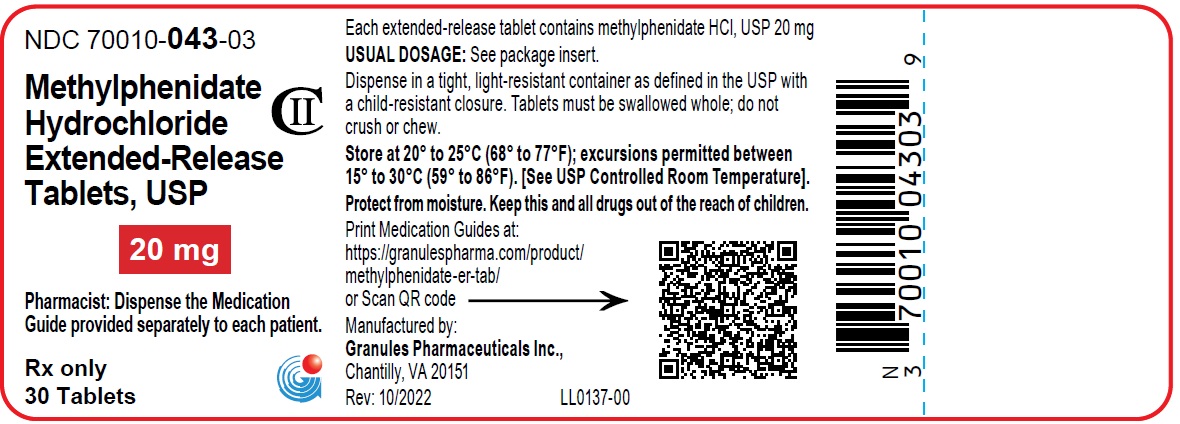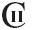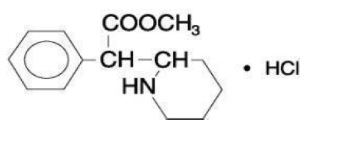 DRUG LABEL: METHYLPHENIDATE HYDROCHLORIDE
NDC: 70010-042 | Form: TABLET, EXTENDED RELEASE
Manufacturer: Granules Pharmaceuticals Inc.
Category: prescription | Type: HUMAN PRESCRIPTION DRUG LABEL
Date: 20251014
DEA Schedule: CII

ACTIVE INGREDIENTS: METHYLPHENIDATE HYDROCHLORIDE 10 mg/1 1
INACTIVE INGREDIENTS: HYPROMELLOSE 2208 (15000 MPA.S); MICROCRYSTALLINE CELLULOSE; LACTOSE MONOHYDRATE; SILICON DIOXIDE; MAGNESIUM STEARATE

HIGHLIGHTS OF PRESCRIBING INFORMATION

Methylphenidate hydrochloride extended-release tablets, USP
These highlights do not include all the information needed to use METHYLPHENIDATE HYDROCHLORIDE EXTENDED-RELEASE TABLETS safely and effectively. See full prescribing information for METHYLPHENIDATE HYDROCHLORIDE EXTENDED-RELEASE TABLETS.
METHYLPHENIDATE HYDROCHLORIDE extended-release tablets, for oral use, CII
Initial U.S. Approval: 1955

WARNING: ABUSE AND DEPENDENCE

WARNING: ABUSE AND DEPENDANCE

See full prescribing information for complete boxed warning.

- CNS stimulants, including Methylphenidate hydrochloride extended-release tablets, other methylphenidate-containing products, and amphetamine, have a high potential for abuse and dependence (5.1, 9.2, 9.3).
- Assess the risk of abuse prior to prescribing, and monitor for signs of abuse and dependence while on therapy (5.1, 9.2)

1 INDICATIONS AND USAGE

Methylphenidate hydrochloride extended-release tablet is a central nervous system (CNS) stimulant indicated for the treatment of Attention Deficit Hyperactivity Disorders (ADHD) and Narcolepsy (1).

Limitations of Use

The use of methylphenidate hydrochloride extended-release tablets are not recommended in pediatric patients younger than 6 years of age because they had higher plasma exposure and a higher incidence of adverse reactions (e.g., weight loss) than patients 6 years and older at the same dosage (5.7, 8.4).

2 DOSAGE AND ADMINISTRATION

Methylphenidate hydrochloride extended-release tablets (2.2):

- May switch to Methylphenidate hydrochloride extended-release tablets when the 8-hour dosage of Methylphenidate hydrochloride extended-release tablets corresponds to the titrated 8-hour dosage of methylphenidate hydrochloride tablets.
- Must be swallowed whole and never crushed or chewed.

3 DOSAGE FORMS AND STRENGTHS

Extended-release Tablets: 10 mg and 20 mg (3)

4 CONTRAINDICATIONS

- Known hypersensitivity to methylphenidate or other product components of Methylphenidate hydrochloride extended-release tablets. (4)

- Concurrent treatment with a monoamine oxidase inhibitor (MAOI), or use of an MAOI within the preceding 14 days (4).

5 WARNINGS AND PRECAUTIONS

- Serious Cardiovascular Events: Sudden death has been reported in association with CNS-stimulant treatment at usual doses in pediatric patients with structural cardiac abnormalities or other serious heart problems. In adults, sudden death, stroke, and myocardial infarction have been reported. Avoid use in patients with known structural cardiac abnormalities, cardiomyopathy, serious heart rhythm arrhythmias, or coronary artery disease (5.2).
- Blood Pressure and Heart Rate Increases: Monitor blood pressure and pulse. Consider the benefits and risk in patients for whom an increase in blood pressure or heart rate would be problematic (5.3).
- Psychiatric Adverse Reactions: Use of stimulants may cause psychotic or manic symptoms in patients with no prior history or exacerbation of symptoms in patients with pre-existing psychiatric illness. Evaluate for pre-existing psychotic or bipolar disorder prior to Methylphenidate hydrochloride extended-release tablets use (5.4).
- Priapism: Cases of painful and prolonged penile erections, and priapism have been reported with methylphenidate products. Immediate medical attention should be sought if signs or symptoms of prolonged penile erections or priapism are observed (5.5).
- Peripheral Vasculopathy, including Raynaud’s Phenomenon: Stimulants used to treat ADHD are associated with peripheral vasculopathy, including Raynaud’s phenomenon. Careful observation for digital changes is necessary during treatment with ADHD stimulants (5.6).
- Long-Term Suppression of Growth: Monitor height and weight at appropriate intervals in pediatric patients (5.7).

6 ADVERSE REACTIONS

Common adverse reactions: tachycardia, palpitations, headache, insomnia, anxiety, hyperhidrosis, weight loss, decreased appetite, dry mouth, nausea, and abdominal pain (6)

To report SUSPECTED ADVERSE REACTIONS, contact Granules Pharmaceuticals Inc. at 1-877-770-3138 or FDA at 1-800-FDA-1088 or www.fda.gov/medwatch.

7 DRUG INTERACTIONS

- Antihypertensive drugs: Monitor blood pressure. Adjust dosage of antihypertensive drug as needed (7)
- Halogenated anesthetics: Avoid use of Methylphenidate hydrochloride extended-release tablets on the day of surgery if halogenated anesthetics will be used (7)
- Risperidone: The combined use of methylphenidate with risperidone when there is a change in dose of either or both medications may increase the risk of extrapyramidal symptoms (EPS). Monitor for signs of EPS (7).

FULL PRESCRIBING INFORMATION

WARNING: ABUSE AND DEPENDENCE

CNS stimulants, including Methylphenidate hydrochloride extended-release tablets, other methylphenidate-containing products, and amphetamines, have a high potential for abuse and dependence. Assess the risk of abuse prior to prescribing, and monitor for signs of abuse and dependence while on therapy [see Warnings and Precautions (5.1), Drug Abuse and Dependence (9.2, 9.3)] .

1 INDICATIONS AND USAGE

Methylphenidate hydrochloride extended-release tablets are indicated for the treatment of:

- Attention Deficit Hyperactivity Disorders (ADHD) in pediatric patients 6 years and older and adults
- Narcolepsy

Limitations of Use

The use of methylphenidate hydrochloride extended-release tablets are not recommended in pediatric patients younger than 6 years of age because they had higher plasma exposure and a higher incidence of adverse reactions (e.g., weight loss) than patients 6 years and older at the same dosage [see Warnings and Precautions (5.7), Use in Specific Populations (8.4)] .

2 DOSAGE AND ADMINISTRATION

N/A

2.1 Pretreatment Screening

Prior to treating pediatric patients and adults with central nervous system (CNS) stimulants, including Methylphenidate hydrochloride extended-release tablets, assess for the presence of cardiac disease (i.e., perform a careful history including family history of sudden death or ventricular arrhythmia, and physical examination) [see Warnings and Precautions (5.2)] .

Assess the risk of abuse prior to prescribing, and monitor for signs of abuse and dependence while on therapy. Maintain careful prescription records, educate patients about abuse, monitor for signs of abuse and overdose, and periodically reevaluate the need for Methylphenidate hydrochloride extended-release tablets use [see Boxed Warning, Warnings and Precautions (5.1), Drug Abuseand Dependence (9)].

2.2 General Dosing Information

Methylphenidate hydrochloride extended-release tablets have a duration of action of approximately 8 hours. Therefore, Methylphenidate hydrochloride extended-release tablets may be used in place of methylphenidate hydrochloride tablets when the 8-hour dosage of Methylphenidate hydrochloride extended-release tablets corresponds to the titrated 8-hour dosage of methylphenidate hydrochloride tablets. Methylphenidate hydrochloride extended-release tablets must be swallowed whole and never crushed or chewed.

Pharmacological treatment of ADHD may be needed for extended periods. Periodically reevaluate the long-term use of Methylphenidate hydrochloride extended-release tablets, and adjust dosage as needed.

2.3 Dose Reduction and Discontinuation

If paradoxical worsening of symptoms or other adverse reactions occur, reduce the dosage, or, if necessary, discontinue Methylphenidate hydrochloride extended-release tablets. If improvement is not observed after appropriate dosage adjustment over a one-month period, the drug should be discontinued.

3 DOSAGE FORMS AND STRENGTHS

- 10 mg extended-release tablets, white to off white, round shaped, uncoated, tablets debossed with “FM4” on one side and plain on other side.
- 20 mg extended-release tablets, white to off white, round shaped, uncoated, tablets debossed with “FM5” on one side and plain on other side.

4 CONTRAINDICATIONS

- Hypersensitivity to methylphenidate or other components of Methylphenidate hydrochloride extended-release tablets. Hypersensitivity reactions such as angioedema and anaphylactic reactions have been reported in patients treated with methylphenidate [ see Adverse Reactions (6)].
- Concomitant treatment with monoamine oxidase inhibitors (MAOIs), or within 14 days following discontinuation of treatment with an MAOI, because of the risk of hypertensive crises [ see Drug Interactions (7.1)].

5 WARNINGS AND PRECAUTIONS

N/A

5.1 Potential for Abuse and Dependence

CNS stimulants, including Methylphenidate hydrochloride extended-release tablets other methylphenidate-containing products, and amphetamines, have a high potential for abuse and dependence. Assess the risk of abuse prior to prescribing, and monitor for signs of abuse and dependence while on therapy [see Boxed Warning, Drug Abuse and Dependence (9.2, 9.3)].

5.2 Serious Cardiovascular Reactions

Sudden death, stroke and myocardial infarction have been reported in adults with CNS stimulant treatment at recommended doses. Sudden death has been reported in pediatric patients with structural cardiac abnormalities and other serious heart problems taking CNS stimulants at recommended doses for ADHD. Avoid use in patients with known serious structural cardiac abnormalities, cardiomyopathy, serious heart rhythm abnormalities, coronary artery disease, and other serious heart problems. Further evaluate patients who develop exertional chest pain, unexplained syncope, or arrhythmias during Methylphenidate hydrochloride extended-release tablets treatment.

5.3 Blood Pressure and Heart Rate Increases

CNS stimulants cause an increase in blood pressure (mean increase approximately 2 to 4 mmHg) and heart rate (mean increase approximately 3 to 6 bpm). Individuals may have larger increases. Monitor all patients for hypertension and tachycardia.

5.4 Psychiatric Adverse Reactions

Exacerbation of Preexisting Psychosis

CNS stimulants may exacerbate symptoms of behavior disturbance and thought disorder in patients with a preexisting psychotic disorder.

Induction of a Manic Episode in Patients with Bipolar Disorder

CNS stimulants may induce a manic or mixed mood episode in patients. Prior to initiating treatment, screen patients for risk factors for developing a manic episode (e.g., comorbid or history of depressive symptoms or a family history of suicide, bipolar disorder, or depression).

New Psychotic or Manic Symptoms

CNS stimulants, at recommended doses, may cause psychotic or manic symptoms (e.g., hallucinations, delusional thinking, or mania) in patients without a prior history of psychotic illness or mania. If such symptoms occur, consider discontinuing Methylphenidate hydrochloride extended-release tablets. In a pooled analysis of multiple short-term, placebo-controlled studies of CNS stimulants, psychotic or manic symptoms occurred in approximately 0.1% of CNS stimulant-treated patients, compared to 0 in placebo-treated patients.

5.5 Priapism

Prolonged and painful erections, sometimes requiring surgical intervention, have been reported with methylphenidate products in both pediatric and adult patients. Priapism was not reported with drug initiation but developed after some time on the drug, often subsequent to an increase in dose. Priapism has also appeared during a period of drug withdrawal (drug holidays or during discontinuation). Patients who develop abnormally sustained or frequent and painful erections should seek immediate medical attention.

5.6 Peripheral Vasculopathy, including Raynaud’s Phenomenon

CNS stimulants, including Methylphenidate hydrochloride extended-release tablets used to treat ADHD are associated with peripheral vasculopathy, including Raynaud’s phenomenon. Signs and symptoms are usually intermittent and mild; however, very rare sequelae include digital ulceration and/or soft tissue breakdown. Effects of peripheral vasculopathy, including Raynaud’s phenomenon, were observed in postmarketing reports at different times and at therapeutic doses in all age groups throughout the course of treatment. Signs and symptoms generally improve after reduction in dose or discontinuation of drug. Careful observation for digital changes is necessary during treatment with ADHD stimulants. Further clinical evaluation (e.g., rheumatology referral) may be appropriate for certain patients.

5.7 Long-Term Suppression of Growth in Pediatric Patients

Methylphenidate hydrochloride extended-release tablets are not approved for use and are not recommended in pediatric patients below 6 years of age [see Use in Specific Populations (8.4)] .

CNS stimulants have been associated with weight loss and slowing of growth rate in pediatric patients.

Careful follow-up of weight and height in pediatric patients ages 7 to 10 years who were randomized to either methylphenidate or non-medication treatment groups over 14 months, as well as in naturalistic subgroups of newly methylphenidate-treated and non-medication treated patients over 36 months (to the ages of 10 to 13 years), suggests that consistently medicated pediatric patients (i.e., treatment for 7 days per week throughout the year) have a temporary slowing in growth rate (on average, a total of about 2 cm less growth in height and 2.7 kg less growth in weight over 3 years), without evidence of growth rebound during this period of development.

Closely monitor growth (weight and height) in pediatric patients treated with CNS stimulants including Methylphenidate hydrochloride extended-release tablets. Patients who are not growing or gaining height or weight as expected may need to have their treatment interrupted.

6 ADVERSE REACTIONS

The following are discussed in more detail in other sections of the labeling:

- Abuse and Dependence [see Boxed Warning, Warnings and Precautions (5.1), Drug Abuse and Dependence (9.2, 9.3)]
- Known hypersensitivity to methylphenidate or other ingredients of Methylphenidate hydrochloride extended-release tablets [ see Contraindications (4)]
- Hypertensive crisis with Concomitant Use of Monoamine Oxidase Inhibitors [see Contraindications (4), Drug Interactions (7.1)]
- Serious Cardiovascular Reactions [see Warnings and Precautions (5.2)]
- Blood Pressure and Heart Rate Increases [see Warnings and Precautions (5.3)]
- Psychiatric Adverse Reactions [see Warnings and Precautions (5.4)]
- Priapism [see Warnings and Precautions (5.5)]
- Peripheral Vasculopathy, including Raynaud’s Phenomenon [see Warnings and Precautions (5.6)]
- Long-term Suppression of Growth [see Warnings and Precautions (5.7)]

The following adverse reactions associated with the use of all Methylphenidate hydrochloride extended-release tablets and other methylphenidate products were identified in clinical trials, spontaneous reports, and literature. Because these reactions were reported voluntarily from a population of uncertain size, it is not always possible to estimate their frequency reliably or to establish a causal relationship to drug exposure.

Adverse Reactions Reported with Methylphenidate hydrochloride extended-release tablets

Infections and Infestations: nasopharyngitis

Blood and the Lymphatic System Disorders :leukopenia, thrombocytopenia, anemia

Immune System Disorders: hypersensitivity reactions, including angioedema and anaphylaxis

Metabolism and Nutrition Disorders: decreased appetite, reduced weight gain, and suppression of growth during prolonged use in pediatric patients

Psychiatric Disorders: insomnia, anxiety, restlessness, agitation, psychosis (sometimes with visual and tactile hallucinations), depressed mood

Nervous System Disorders: headache, dizziness, tremor, dyskinesia including choreoathetoid movements, drowsiness, convulsions, cerebrovascular disorders (including vasculitis, cerebral hemorrhages and cerebrovascular accidents), serotonin syndrome in combination with serotonergic drugs

Eye Disorders: blurred vision, difficulties in visual accommodation

Cardiac Disorders: tachycardia, palpitations, increased blood pressure, arrhythmias, angina pectoris

Respiratory, Thoracic and Mediastinal Disorders: cough

Gastrointestinal Disorders: dry mouth, nausea, vomiting, abdominal pain, dyspepsia

Hepatobiliary Disorders: abnormal liver function, ranging from transaminase elevation to severe hepatic injury

Skin and Subcutaneous Tissue Disorders: hyperhidrosis, pruritus, urticaria, exfoliative dermatitis, scalp hair loss, erythema multiforme rash, thrombocytopenic purpura

Musculoskeletal and Connective Tissue Disorders: arthralgia, muscle cramps, rhabdomyolysis

Investigations: weight loss (adult ADHD patients)

Additional Adverse Reactions Reported with Other Methylphenidate-Containing Products

The list below shows adverse reactions not listed for Methylphenidate hydrochloride extended-release tablets that have been reported with other methylphenidate-containing products.

Blood and Lymphatic Disorders: pancytopenia

Immune System Disorders: hypersensitivity reactions such as auricular swelling, bullous conditions, eruptions, exanthemas

Psychiatric Disorders: affect lability, mania, disorientation and libido changes

Nervous System Disorders: migraine

Eye Disorders: diplopia, mydriasis

Cardiac Disorders: sudden cardiac death, myocardial infarction, bradycardia, extrasystole

Vascular Disorders: peripheral coldness, Raynaud's phenomenon

Respiratory, Thoracic and Mediastinal Disorders: pharyngolaryngeal pain, dyspnea

Gastrointestinal Disorders: diarrhea, constipation

Skin and Subcutaneous Tissue Disorders: angioneurotic edema, erythema, fixed drug eruption

Musculoskeletal, Connective Tissue and bone Disorders: myalgia, muscle twitching

Renal and Urinary Disorders: hematuria

Reproductive System and Breast Disorders: gynecomastia

General Disorders: fatigue, hyperpyrexia

Urogenital Disorders: priapism

7 DRUG INTERACTIONS

N/A

7.1 Clinically Important Interactions with Methylphenidate hydrochloride extended-release tablets

Table 1 presents clinically important drug interactions with Methylphenidate hydrochloride extended-release tablets.

Table 1: Clinically Important Drug Interactions with Methylphenidate Hydrochloride Extended-Release Tablets

Monoamine Oxidase Inhibitors (MAOI)
Clinical Impact | Concomitant use of MAOIs and CNS stimulants, including Methylphenidate hydrochloride extended-release tablets can cause hypertensive crisis. Potential outcomes include death, stroke, myocardial infarction, aortic dissection, ophthalmological complications, eclampsia, pulmonary edema, and renal failure [ see Contraindications (4)] .
Intervention | Concomitant use of Methylphenidate hydrochloride extended-release tablets with MAOIs or within 14 days after discontinuing MAOI treatment is contraindicated.
Examples | selegiline, tranylcypromine, isocarboxazid, phenelzine, linezolid, methylene blue
Antihypertensive Drugs
Clinical Impact | Methylphenidate hydrochloride extended-release tablets may decrease the effectiveness of drugs used to treat hypertension [ see Warnings and Precautions (5.3)] .
Intervention | Monitor blood pressure and adjust the dosage of the antihypertensive drug as needed.
Examples | Potassium-sparing and thiazide diuretics, calcium channel blockers, angiotensin-converting-enzyme (ACE) inhibitors, angiotensin II receptor blockers (ARBs), beta blockers, centrally acting alpha-2 receptor agonists
Halogenated Anesthetics
Clinical Impact | Concomitant use of halogenated anesthetics and Methylphenidate hydrochloride extended-release tablets may increase the risk of sudden blood pressure and heart rate increase during surgery.
Intervention | Avoid use of Methylphenidate hydrochloride extended-release tablets in patients being treated with anesthetics on the day of surgery.
Examples | halothane, isoflurane, enflurane, desflurane, sevoflurane
Risperidone
 | The combined use of methylphenidate with risperidone when there is a change in dose of either or both medications may increase the risk of extrapyramidal symptoms (EPS). Monitor for signs of EPS.

8 USE IN SPECIFIC POPULATIONS

N/A

8.1 Pregnancy

Pregnancy Exposure Registry

There is a pregnancy exposure registry that monitors pregnancy outcomes in women exposed to ADHD medications, including Methylphenidate hydrochloride extended-release tablets, during pregnancy. Healthcare providers are encouraged to register patients by calling the National Pregnancy Registry for ADHD Medications at 1-866-961-2388 or visit https://womensmentalhealth.org/adhd-medications/

Risk Summary

Published studies and postmarketing reports on methylphenidate use during pregnancy have not identified a drug-associated risk of major birth defects, miscarriage or adverse maternal or fetal outcomes. There may be risks to the fetus associated with the use of CNS stimulants use during pregnancy [see Clinical Considerations].

No effects on morphological development were observed in embryo-fetal development studies with oral administration of methylphenidate to pregnant rats and rabbits during organogenesis at doses up to 10 and 15 times, respectively, the maximum recommended human dose (MRHD) of 60 mg/day given to adolescents on a mg/m^2basis. However, spina bifida was observed in rabbits at a dose 52 times the MRHD given to adolescents. A decrease in pup body weight was observed in a pre- and post-natal development study with oral administration of methylphenidate to rats throughout pregnancy and lactation at doses 6 times the MRHD given to adolescents (see Data).

The estimated background risk of major birth defects and miscarriage for the indicated population is unknown. All pregnancies have a background risk of birth defect, loss, or other adverse outcomes. In the U.S. general population, the estimated background risk of major birth defects and miscarriage in clinically recognized pregnancies is 2% to 4% and 15% to 20%, respectively.

Clinical Considerations

Fetal/Neonatal Adverse Reactions

CNS stimulants, such as Methylphenidate hydrochloride extended-release tablets, can cause vasoconstriction and thereby decrease placental perfusion. No fetal and/or neonatal adverse reactions have been reported with the use of therapeutic doses of methylphenidate during pregnancy; however, premature delivery and low birth weight infants have been reported in amphetamine-dependent mothers.

Data

Animal Data

In embryo-fetal development studies conducted in rats and rabbits, methylphenidate was administered orally at doses of up to 75 and 200 mg/kg/day, respectively, during the period of organogenesis. Malformations (increased incidence of fetal spina bifida) were observed in rabbits at the highest dose, which is approximately 52 times the MRHD of 60 mg/day given to adolescents on a mg/m^2basis. The no effect level for embryo-fetal development in rabbits was 60 mg/kg/day (15times the MRHD given to adolescents on a mg/m^2basis). There was no evidence of morphological development effects in rats, although increased incidences of fetal skeletal variations were seen at the highest dose level (10 times the MRHD of 60 mg/day given to adolescents on a mg/m^2basis), which was also maternally toxic. The no effect level for embryo-fetal development in rats was 25 mg/kg/day (3 times the MRHD on a mg/m^2basis). When methylphenidate was administered to rats throughout pregnancy and lactation at doses of up to 45 mg/kg/day, offspring body weight gain was decreased at the highest dose (6 times the MRHD of 60 mg/day given to adolescents on a mg/m^2basis), but no other effects on postnatal development were observed. The no effect level for pre- and postnatal development in rats was 15 mg/kg/day (~2 times the MRHD given to adolescents on a mg/m^2basis).

8.2 Lactation

Risk Summary

Limited published literature, based on milk sampling from seven mothers reports that methylphenidate is present in human milk, which resulted in infant doses of 0.16% to 0.7% of the maternal weight-adjusted dosage and a milk/plasma ratio ranging between 1.1 and 2.7. There are no reports of adverse effects on the breastfed infant and no effects on milk production. Long-term neurodevelopmental effects on infants from stimulant exposure are unknown. The developmental and health benefits of breastfeeding should be considered along with the mother’s clinical need for Methylphenidate hydrochloride extended-release tablets and any potential adverse effects on the breastfed infant from Methylphenidate hydrochloride extended-release tablets or from the underlying maternal condition.

Clinical Considerations

Monitor breastfeeding infants for adverse reactions, such as agitation, insomnia, anorexia, and reduced weight gain.

8.4 Pediatric Use

The safety and effectiveness of methylphenidate hydrochloride extended-release tablets have not been established in pediatric patients below the age of 6 years.

In studies evaluating extended-release methylphenidate products, patients 4 to <6 years of age had higher systemic methylphenidate exposures than those observed in older pediatric patients at the same dosage. Pediatric patients 4 to <6 years of age also had a higher incidence of adverse reactions, including weight loss.

The safety and effectiveness of Methylphenidate hydrochloride extended-release tablets for the treatment of ADHD have been established in pediatric patients 6 to 17 years.

The long-term efficacy of Methylphenidate hydrochloride extended-release tablets in pediatric patients has not been established.

Long-Term Suppression of Growth

Growth should be monitored during treatment with stimulants, including Methylphenidate hydrochloride extended-release tablets. Pediatric patients who are not growing or gaining weight as expected may need to have their treatment interrupted [ see Warnings and Precautions (5.7)] .

Juvenile Animal Toxicity Data

Rats treated with methylphenidate early in the postnatal period through sexual maturation demonstrated a decrease in spontaneous locomotor activity in adulthood. A deficit in acquisition of a specific learning task was observed in females only. The doses at which these findings were observed are at least 4 times the MRHD of 60 mg/day given to children on a mg/m^2 basis.

In a study conducted in young rats, methylphenidate was administered orally at doses of up to 100 mg/kg/day for 9 weeks, starting early in the postnatal period (postnatal Day 7) and continuing through sexual maturity (postnatal Week 10). When these animals were tested as adults (postnatal Weeks 13 to 14), decreased spontaneous locomotor activity was observed in males and females previously treated with 50 mg/kg/day (approximately 4 times the MRHD of 60 mg/day given to children on a mg/m^2 basis) or greater, and a deficit in the acquisition of a specific learning task was seen in females exposed to the highest dose (8 times the MRHD given to children on a mg/m^2 basis). The no effect level for juvenile neurobehavioral development in rats was 5 mg/kg/day (approximately 0.5 times the MRHD given to children on a mg/m^2 basis). The clinical significance of the long-term behavioral effects observed in rats is unknown.

8.5 Geriatric Use

Methylphenidate hydrochloride tablet has not been studied in the geriatric population.

9 DRUG ABUSE AND DEPENDENCE

N/A

9.1 Controlled Substance

Methylphenidate hydrochloride extended-release tablets contain methylphenidate hydrochloride, a Schedule II controlled substance.

9.2 Abuse

CNS stimulants, including Methylphenidate hydrochloride extended-release tablets have a high potential for abuse. Abuse is characterized by impaired control over drug use despite harm, and craving.

Signs and symptoms of CNS stimulant abuse include increased heart rate, respiratory rate, blood pressure, and/or sweating, dilated pupils, hyperactivity, restlessness, insomnia, decreased appetite, loss of coordination, tremors, flushed skin, vomiting, and/or abdominal pain. Anxiety, psychosis, hostility, aggression, and suicidal or homicidal ideation have also been observed. Abusers of CNS stimulants may chew, snort, inject, or use other unapproved routes of administration which may result in overdose and death [ see Overdosage (10)] .

To reduce the abuse of CNS stimulants including Methylphenidate hydrochloride extended-release tablets assess the risk of abuse prior to prescribing. After prescribing, keep careful prescription records, educate patients and their families about abuse and on proper storage and disposal of CNS stimulants [ see How Supplied/Storage and Handling (16)] , monitor for signs of abuse while on therapy, and reevaluate the need for Methylphenidate hydrochloride extended-release tablets use.

9.3 Dependence

Tolerance

Tolerance (a state of adaptation in which exposure to a drug results in a reduction of the drug’s desired and/or undesired effects over time) can occur during chronic therapy with CNS stimulants, including Methylphenidate hydrochloride extended-release tablets.

Dependence

Physical dependence (which is manifested by a withdrawal syndrome produced by abrupt cessation, rapid dose reduction, or administration of an antagonist) may occur in patients treated with CNS stimulants including Methylphenidate hydrochloride extended-release tablets. Withdrawal symptoms after abrupt cessation following prolonged high-dosage administration of CNS stimulants include dysphoric mood; fatigue; vivid, unpleasant dreams; insomnia or hypersomnia; increased appetite; and psychomotor retardation or agitation.

10 OVERDOSAGE

Human Experience

Signs and symptoms of acute overdosage, resulting principally from overstimulation of the central nervous system and from excessive sympathomimetic effects, may include the following: nausea, vomiting, diarrhea, restlessness, anxiety, agitation, tremors, hyperreflexia, muscle twitching, convulsions (which may be followed by coma), euphoria, confusion, hallucinations, delirium, sweating, flushing, headache, hyperpyrexia, tachycardia, palpitations, cardiac arrhythmias, hypertension, hypotension, tachypnea, mydriasis, dryness of mucous membranes, and rhabdomyolysis.

Overdose Management

Consult with a Certified Poison Control Center (1-800-222-1222) for the latest recommendations.

11 DESCRIPTION

Methylphenidate hydrochloride extended-release tablets, USP contains methylphenidate hydrochloride a CNS stimulant. It is available as extended-release tablets of 10 mg and 20 mg strength for oral administration. Methylphenidate hydrochloride is methyl α-phenyl-2-piperidineacetate hydrochloride, and its structural formula is:

Methylphenidate hydrochloride USP is a white, odorless, fine crystalline powder. Its solutions are acid to litmus. It is freely soluble in water and in methanol, soluble in alcohol, and slightly soluble in chloroform and in acetone. Its molecular weight is 269.77 g/mol.

Methylphenidate hydrochloride extended-release tablets, USP contains the following inactive ingredients: hypromellose, microcrystalline cellulose, lactose monohydrate, colloidal silicon dioxide and magnesium stearate.

FDA approved dissolution test differs from the USP dissolution test.

12 CLINICAL PHARMACOLOGY

N/A

12.1 Mechanism of Action

Methylphenidate hydrochloride is a central nervous system (CNS) stimulant. The mode of therapeutic action in ADHD and narcolepsy is not known.

12.2 Pharmacodynamics

Methylphenidate is a racemic mixture comprised of the d- and l-threo enantiomers. The d-threo enantiomer is more pharmacologically active than the l-threo enantiomer. Methylphenidate blocks the reuptake of norepinephrine and dopamine into the presynaptic neuron and increase the release of these monoamines into the extraneuronal space.

Cardiac Electrophysiology

A formal QT study has not been conducted in patients taking Methylphenidate hydrochloride extended-release tablets.

The effect of dexmethylphenidate, the pharmacologically active d-enantiomer of Methylphenidate hydrochloride tablets on the QT interval was evaluated in a double-blind, placebo- and open-label active (moxifloxacin)-controlled study following single doses of dexmethylphenidate XR 40 mg (maximum recommended adult total daily dosage) in 75 healthy volunteers. Electrocardiograms (ECGs) were collected up to 12 hours postdose. Frederica’s method for heart rate correction was employed to derive the corrected QT interval (QTcF). The maximum mean prolongation of QTcF intervals was less than 5 ms, and the upper limit of the 90% confidence interval (CI) was below 10 ms for all time-matched comparisons versus placebo. This was below the threshold of clinical concern and there was no evident exposure response relationship.

12.3 Pharmacokinetics

Absorption

Methylphenidate hydrochloride in the extended-release tablets is more slowly but as extensively absorbed as in the regular tablets. Relative bioavailability of the extended-release tablet compared to the Methylphenidate hydrochloride tablet measured by the urinary excretion of Methylphenidate hydrochloride major metabolite (α-phenyl-2-piperidine acetic acid) was 105% (49% to 168%) in children and 101% (85% to 152%) in adults. The time to peak rate in children was 1.9 hours (0.3 to 4.4 hours) for the Methylphenidate hydrochloride tablets and 4.7 hours (1.3 to 8.2 hours) for the Methylphenidate hydrochloride extended-release tablets. An average of 67% of extended-release tablet dose was excreted in children as compared to 86% in adults.

Effect of Food

After a high-fat meal, both area under the curve (AUC) (by 25%) and Cmax(by 27%) are higher. Time to Cmax (Tmax) is faster after a high-fat meal (median Tmax: 2.5 hours) as compared to without food (median Tmax: 3 hours).

Distribution

Binding to plasma proteins is low (10% to 33%). The volume of distribution was 2.65 ± 1.11 L/kg for d-methylphenidate and 1.80 ± 0.91 L/kg for l-methylphenidate.

Elimination

The systemic clearance is 0.40 ± 0.12 L/h/kg for d-methylphenidate and 0.73 ± 0.28 L/h/kg for l-methylphenidate.

Metabolism

Methylphenidate is metabolized primarily by de-esterification to alpha-phenyl-piperidine acetic acid (ritalinic acid), which has little or no pharmacologic activity.

Excretion

After oral administration, 78% to 97% of the dose is excreted in the urine and 1% to 3% in feces in the form of metabolites within 48 to 96 hours. Most of the dose is excreted in the urine as alpha-phenyl-2-piperidine acetic acid (60% to 86%). The cumulative urinary excretion of alpha-phenyl-2-piperidine acetic acid are not significantly different for Methylphenidate hydrochloride extended-release tablets.

Studies in Specific Populations

Male and Female Patients

In a clinical study involving adult subjects who received Methylphenidate hydrochloride extended-release tablets plasma concentrations of Methylphenidate hydrochloride's major metabolite appeared to be greater in females than in males. No gender differences were observed for Methylphenidate hydrochloride plasma concentration in the same subjects.

Racial or Ethnic Groups

There is insufficient experience with the use of Methylphenidate hydrochloride extended-release to detect ethnic variations in pharmacokinetics.

Patients with Renal Impairment

Methylphenidate hydrochloride has not been studied in renally-impaired patients. Renal impairment is expected to have minimal effect on the pharmacokinetics of methylphenidate since less than 1% of a radiolabeled dose is excreted in the urine as unchanged compound, and the major metabolite (ritalinic acid), has little or no pharmacologic activity.

Patients with Hepatic Impairment

Methylphenidate hydrochloride has not been studied in patients with hepatic impairment. Hepatic impairment is expected to have minimal effect on the pharmacokinetics of methylphenidate since it is metabolized primarily to ritalinic acid by nonmicrosomal hydrolytic esterases that are widely distributed throughout the body.

13 NONCLINICAL TOXICOLOGY

N/A

13.1 Carcinogenesis, Mutagenesis, and Impairment of Fertility

Carcinogenesis

In a lifetime carcinogenicity study carried out in B6C3F1 mice, methylphenidate caused an increase in hepatocellular adenomas, and in males only, an increase in hepatoblastomas at a daily dose of approximately 60 mg/kg/day. This dose is approximately 2 times the MRHD of 60 mg/day given to children on mg/m^2 basis. Hepatoblastoma is a relatively rare rodent malignant tumor type. There was no increase in total malignant hepatic tumors. The mouse strain used is sensitive to the development of hepatic tumors and the significance of these results to humans is unknown.

Methylphenidate did not cause any increase in tumors in a lifetime carcinogenicity study carried out in F344 rats; the highest dose used was approximately 45 mg/kg/day, which is approximately 4 times the MRHD (children) on a mg/m^2 basis.

In a 24-week carcinogenicity study in the transgenic mouse strain p53+/-, which is sensitive to genotoxic carcinogens, there was no evidence of carcinogenicity. Male and female mice were fed diets containing the same concentration of methylphenidate as in the lifetime carcinogenicity study; the high-dose groups were exposed to 60 to 74 mg/kg/day of methylphenidate.

Mutagenesis

Methylphenidate was not mutagenic in the in vitro Ames reverse mutation assay, in the in vitro mouse lymphoma cell forward mutation assay, or in the in vitro chromosomal aberration assay using human lymphocytes. Sister chromatid exchanges and chromosome aberrations were increased, indicative of a weak clastogenic response, in an in vitro assay in cultured Chinese Hamster Ovary (CHO) cells. Methylphenidate was negative in vivo in males and females in the mouse bone marrow micronucleus assay.

Impairment of Fertility

No human data on the effect of methylphenidate on fertility are available. Methylphenidate did not impair fertility in male or female mice that were fed diets containing the drug in an 18-week continuous breeding study. The study was conducted at doses up to 160 mg/kg/day, approximately 10 times the MRHD of 60 mg/day given to adolescents on a mg/m^2 basis.

16 HOW SUPPLIED/STORAGE AND HANDLING

Methylphenidate hydrochloride extended-release tablets, USP are available as follows:

10 mg: White to off white, round shaped, uncoated, tablets debossed with “FM4” on one side and plain on other side.

Bottles of 30 tablets NDC 70010-042-03
Bottles of 100 tablets NDC 70010-042-01

20 mg: White to off white, round shaped, uncoated, tablets debossed with “FM5” on one side and plain on other side.

Bottles of 30 tablets NDC 70010-043-03
Bottles of 100 tablets NDC 70010-043-01

NOTE: Methylphenidate hydrochloride extended-release tablets, USP are color-additive free.

Store at 20°C to 25°C (68°F to 77°F); excursions permitted between 15°C to 30°C (59°F to 86°F) [See USP Controlled Room Temperature].

Protect from moisture.

Dispense in a tight, light-resistant container as defined in the USP, with a child-resistant closure.

Disposal

Comply with local laws and regulations on drug disposal of CNS stimulants. Dispose of remaining, unused, or expired Methylphenidate hydrochloride extended-release tablets, USP by a medicine takeback program or by an authorized collector registered with the Drug Enforcement Administration. If no take-back program or authorized collector is available, mix Methylphenidate hydrochloride extended-release tablets, USP with an undesirable, nontoxic substance to make it less appealing to children and pets. Place the mixture in a container such as a sealed plastic bag and discard Methylphenidate hydrochloride extended-release tablets, USP in the household trash.

17 PATIENT COUNSELING INFORMATION

Advise the patient to read the FDA-approved patient labeling (Medication Guide).

Controlled Substance Status/High Potential for Abuse and Dependence

Advise patients that Methylphenidate hydrochloride extended-release tablets are controlled substances, and they can be abused and lead to dependence. Instruct patients that they should not give Methylphenidate hydrochloride extended-release tablets to anyone else. Advise patients to store Methylphenidate hydrochloride extended-release tablets in a safe place, preferably locked, to prevent abuse. Advise patients to comply with laws and regulations on drug disposal. Advise patients to dispose of remaining, unused, or expired Methylphenidate hydrochloride extended-release tablets by a medicine take-back program if available [see Boxed Warning, Warnings and Precautions (5.1), Drug Abuse and Dependence (9.1,9.2,9.3), How Supplied/Storage and Handling (16)] .

Serious Cardiovascular Risks

Advise patients that there is a potential serious cardiovascular risk including sudden death, myocardial infarction, stroke, and hypertension with Methylphenidate hydrochloride extended-release tablets use. Instruct patients to contact a healthcare provider immediately if they develop symptoms such as exertional chest pain, unexplained syncope, or other symptoms suggestive of cardiac disease [ see Warnings and Precautions (5.2)].

Blood Pressure and Heart Rate Increases

Instruct patients that Methylphenidate hydrochloride extended-release tablets can cause elevations of their blood pressure and pulse rate [ see Warnings and Precautions (5.3)] .

Psychiatric Risks

Advise patients that Methylphenidate hydrochloride extended-release tablets at recommended doses, can cause psychotic or manic symptoms, even in patients without prior history of psychotic symptoms or mania [ see Warnings and Precautions (5.4)].

Priapism

Advise patients of the possibility of painful or prolonged penile erections (priapism). Instruct them to seek immediate medical attention in the event of priapism [ see Warnings and Precautions (5.5)] .

Circulation Problems in Fingers and Toes [Peripheral vasculopathy, including Raynaud’s Phenomenon]

Instruct patients about the risk of peripheral vasculopathy, including Raynaud’s phenomenon, and associated signs and symptoms: fingers or toes may feel numb, cool, painful, and/or may change color from pale, to blue, to red. Instruct patients to report to their physician any new numbness, pain, skin color change, or sensitivity to temperature in fingers or toes.

Instruct patients to call their physician immediately with any signs of unexplained wounds appearing on fingers or toes while taking Methylphenidate hydrochloride extended-release tablets. Further clinical evaluation (e.g., rheumatology referral) may be appropriate for certain patients [ see Warnings and Precautions (5.6)] .

Suppression of Growth

Advise patients that Methylphenidate hydrochloride extended-release tablets may cause slowing of growth and weight loss [ see Warnings and Precautions (5.7)].

Pregnancy Registry

Advise patients that there is a pregnancy exposure registry that monitors pregnancy outcomes in patients exposed to ADHD medications, including Methylphenidate hydrochloride extended-release tablets, during pregnancy [see Use in Specific Populations (8.1)] .

The Medication Guide may also be obtained by calling 877-770-3183.

Manufactured by:

Granules Pharmaceuticals Inc.

Chantilly, VA 20151

Rev. 10/2025

MEDICATION GUIDE

Methylphenidate Hydrochloride Extended-Release Tablets

(meth" il fen' i date hye" droe klor' ide)

What is the most important information I should know about Methylphenidate hydrochloride extended-release tablets?

Methylphenidate hydrochloride extended-release tablets is a federal controlled substance (CII) because it can be abused or lead to dependence. Keep Methylphenidate hydrochloride extended-release tablets in a safe place to prevent misuse and abuse. Selling or giving away Methylphenidate hydrochloride extended-release tablets may harm others and is against the law. Tell your doctor if you or your child have ever abused or been dependent on alcohol, prescription medicines or street drugs.

The following have been reported with use of methylphenidate hydrochloride and other stimulant medicines:

1. Heart-related problems:

- sudden death in patients who have heart problems or heart defects

- stroke and heart attack in adults

- increased blood pressure and heart rate

Tell your doctor if you or your child have any heart problems, heart defects, high blood pressure, or a family history of these problems.

Your doctor should check you or your child carefully for heart problems before starting Methylphenidate hydrochloride extended-release tablets.

Your doctor should check you or your child’s blood pressure and heart rate regularly during treatment with Methylphenidate hydrochloride extended-release tablets.

Call your doctor right away if you or your child has any signs of heart problems such as chest pain, shortness of breath, or fainting while taking Methylphenidate hydrochloride extended-release tablets.

2. Mental (Psychiatric) problems:

All Patients

- new or worse behavior and thought problems

- new or worse bipolar illness

- new or worse aggressive behavior or hostility

- new psychotic symptoms (such as hearing voices, believing things that are not true, are suspicious) or new manic symptoms

Tell your doctor about any mental problems you or your child have, or about a family history of suicide, bipolar illness, or depression.

Call your doctor right away if you or your child have any new or worsening mental symptoms or problems while taking Methylphenidate hydrochloride extended-release tablets, especially seeing or hearing things that are not real, believing things that are not real, or are suspicious.

What is Methylphenidate hydrochloride extended-release tablets?

Methylphenidate hydrochloride extended-release tablet is a central nervous system (CNS) stimulant prescription medicine used for the treatment of Attention Deficit Hyperactivity Disorder (ADHD) in people 6 years of age and older. Methylphenidate hydrochloride extended-release tablets may help increase attention and decrease impulsiveness and hyperactivity in people with ADHD.

Methylphenidate hydrochloride extended-release tablets are not recommended for use in children under 6 years of age with ADHD.

Methylphenidate hydrochloride extended-release tablets should be used as a part of a total treatment program for ADHD that may include counseling or other therapies.

Methylphenidate hydrochloride extended-release tablets are also used in the treatment of a sleep disorder called narcolepsy.

Who should not take Methylphenidate hydrochloride extended-release tablets?

Methylphenidate hydrochloride extended-release tablets should not be taken if you or your child:

- are allergic to methylphenidate hydrochloride, or any of the ingredients in Methylphenidate hydrochloride extended-release tablets. See the end of this Medication Guide for a complete list of ingredients in Methylphenidate hydrochloride extended-release tablets.

- are taking or have taken within the past 14 days an anti-depression medicine called a monoamine oxidase inhibitor or MAOI.

Methylphenidate hydrochloride extended-release tablets may not be right for you or your child. Before starting Methylphenidate hydrochloride extended-release tablets tell you or your child’s doctor about all health conditions (or a family history of) including:

- heart problems, heart defects, high blood pressure
- mental problems including psychosis, mania, bipolar illness, or depression
- circulation problems in fingers or toes
- if you are pregnant or plan to become pregnant. It is not known if Methylphenidate hydrochloride extended-release tablets will harm your unborn baby.
  - There is a pregnancy registry for females who are exposed to ADHD medications, including Methylphenidate hydrochloride extended-release tablets, during pregnancy. The purpose of the registry is to collect information about the health of females exposed to Methylphenidate hydrochloride extended-release tablets and their baby. If you or your child becomes pregnant during treatment with Methylphenidate hydrochloride extended-release tablets talk to your healthcare provider about registering with the National Pregnancy Registry of ADHD Medications at 1-866-961-2388 or visit online at https://womensmentalhealth.org/adhdmedications/.
  - if you are breastfeeding or plan to breastfeed. Methylphenidate hydrochloride passes into your breast milk. Talk to your healthcare provider about the best way to feed your baby during treatment with Methylphenidate hydrochloride extended-release tablets.

Tell your doctor about all of the medicines that you or your child takes including prescription and over-the-counter medicines, vitamins, and herbal supplements. Methylphenidate hydrochloride extended-release tablets and some medicines may interact with each other and cause serious side effects. Sometimes the doses of other medicines will need to be adjusted while taking Methylphenidate hydrochloride extended-release tablets.

Your doctor will decide whether Methylphenidate hydrochloride extended-release tablets can be taken with other medicines.

Especially tell your doctor if you or your child takes:

- anti-depression medicines including MAOIs
- blood pressure medicines (anti-hypertensive)

Know the medicines that you or your child takes. Keep a list of your medicines with you to show your doctor and pharmacist.

Do not start any new medicine while taking Methylphenidate hydrochloride extended-release tabletswithout talking to your doctor first.

How should Methylphenidate hydrochloride extended-release tablets be taken?

- Take Methylphenidate hydrochloride extended-release tablets exactly as prescribed. Your doctor may adjust the dose until it is right for you or your child.

- Take Methylphenidate hydrochloride extended-release tablets 30 to 45 minutes before a meal. The effect of a dose of Methylphenidate hydrochloride extended-release tablets usually lasts about 8 hours.

- Do not chew or crush Methylphenidate hydrochloride extended-release tablets. Swallow Methylphenidate hydrochloride extended-release tablets whole with water or other liquids. Tell your doctor if you or your child cannot swallow Methylphenidate hydrochloride extended-release tablets whole. A different medicine may need to be prescribed.

- From time to time, your doctor may stop Methylphenidate hydrochloride extended-release tablets treatment for a while to check ADHD symptoms.

- Your doctor may do regular checks of the blood, heart, and blood pressure while taking Methylphenidate hydrochloride extended-release tablets.

- Children should have their height and weight checked often while taking Methylphenidate hydrochloride extended-release tablets. Methylphenidate hydrochloride extended-release tablets treatment may be stopped if a problem is found during these check-ups.

- In case of poisoning call your poison control center at 1-800-222-1222 right away or go to the nearest hospital emergency room.

What are the possible side effects of Methylphenidate hydrochloride extended-release tablets?

Methylphenidate hydrochloride extended-release tablets may cause serious side effects, including:

What are possible side effects of Methylphenidate hydrochloride extended-release tablets?

- See “What is the most important information I should know about Methylphenidate hydrochloride extended-release tablets?” for information on reported heart and mental problems.

- painful and prolonged erections (priapism) have occurred with methylphenidate. If you or your child develops priapism, seek medical help right away. Because of the potential for lasting damage, priapism should be evaluated by a doctor immediately.

- circulation problems in fingers and toes (Peripheral vasculopathy, including Raynaud’s phenomenon):
- fingers or toes may feel numb, cool, painful
- fingers or toes may change color from pale, to blue, to red

Tell your doctor if you or your child have numbness, pain, skin color change, or sensitivity to temperature in the fingers or toes.

- Call your doctor right away if you have or your child has any signs of unexplained wounds appearing on fingers or toes while taking Methylphenidate hydrochloride extended-release tablets.

- slowing of growth (height and weight) in children

Common side effects include:

• fast heart beat • abnormal heartbeat (palpitations) • headache • trouble sleeping • nervousness

• sweating a lot • decreased appetite • dry mouth • nausea • stomach pain

Call your doctor for medical advice about side effects. You may report side effects to FDA at 1-800-FDA-1088.

How should I store Methylphenidate hydrochloride extended-release tablets?

- Store Methylphenidate hydrochloride extended-release tablets in a safe place and in a tightly closed container at room temperature between 68°F to 77°F (20°C to 25°C).

- Protect from moisture.

- Dispose of remaining, unused, or expired Methylphenidate hydrochloride extended-release tablets by a medicine take-back program at authorized collection sites such as retail pharmacies, hospital or clinic pharmacies, and law enforcement locations. If no take-back program or authorized collector is available, mix Methylphenidate hydrochloride extended-release tablets with an undesirable, nontoxic substance such as dirt, cat litter, or used coffee grounds to make it less appealing to children and pets. Place the mixture in a container such as a sealed plastic bag and throw away (discard) Methylphenidate hydrochloride extended-release tablets in the household trash.

- Keep Methylphenidate hydrochloride extended-release tablets and all medicines out of the reach of children.

General information about the safe and effective use of Methylphenidate hydrochloride extended-release tablets.

Medicines are sometimes prescribed for purposes other than those listed in a Medication Guide. You can ask your pharmacist or doctor for information about Methylphenidate hydrochloride extended-release tablets that is written for healthcare professionals. Do not use Methylphenidate hydrochloride extended-release tablets for a condition for which it was not prescribed. Do not give Methylphenidate hydrochloride extended-release tablets to other people, even if they have the same symptoms. It may harm them and it is against the law.

What are the ingredients in Methylphenidate hydrochloride extended-release tablets?

Active ingredient: methylphenidate hydrochloride

Inactive ingredients: hypromellose, microcrystalline cellulose, lactose monohydrate, colloidal silicon dioxide and magnesium stearate.

Manufactured by:

Granules Pharmaceuticals Inc.

Chantilly, VA 20151

This Medication Guide has been approved by the U.S. Food and Drug Administration Revised: 10/2025

PRINCIPAL DISPLAY PANEL - 10 mg Tablet Bottle Label

Package Label – 10 mg

NDC 70010-042-03

Methylphenidate Hydrochloride Extended-Release Tablets, USP CII

10 mg

PHARMACIST: Dispense the enclosed Medication Guide to each patient

Rx Only

30 Tablets

PRINCIPAL DISPLAY PANEL - 20 mg Tablet Bottle Label

NDC 70010-043-03

Methylphenidate Hydrochloride Extended-Release Tablets, USP CII

20 mg

PHARMACIST: Dispense the enclosed Medication Guide to each patient

Rx Only

30 Tablets